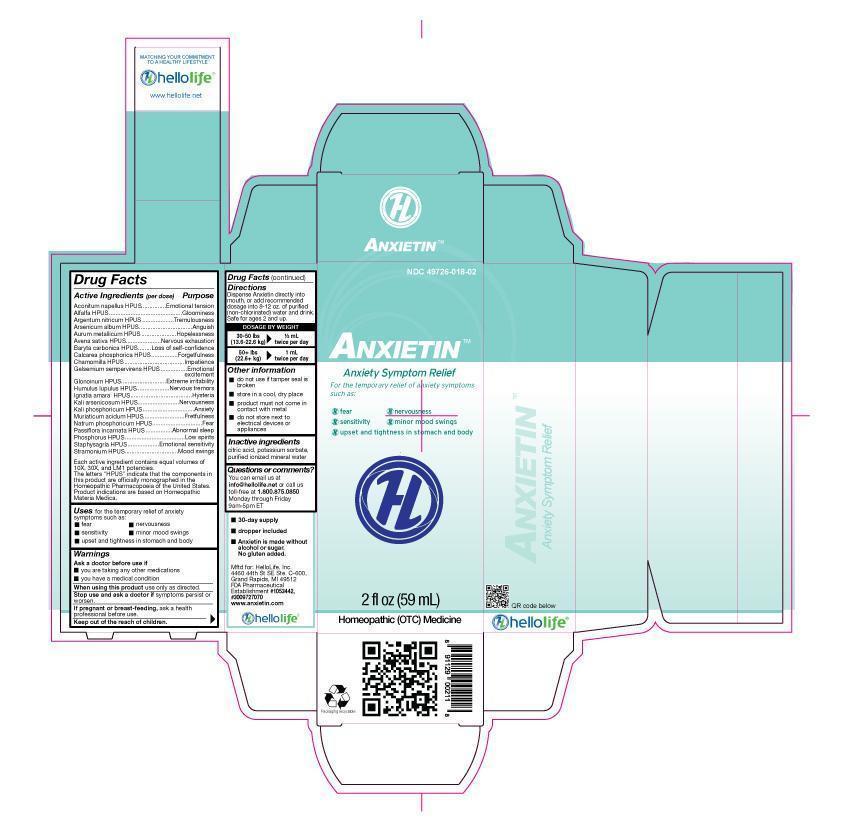 DRUG LABEL: Anxietin
NDC: 49726-018 | Form: LIQUID
Manufacturer: Hello Life, Inc.
Category: homeopathic | Type: HUMAN OTC DRUG LABEL
Date: 20181226

ACTIVE INGREDIENTS: ACONITUM NAPELLUS 10 [hp_X]/59 mL; ALFALFA 10 [hp_X]/59 mL; SILVER NITRATE 10 [hp_X]/59 mL; GOLD 10 [hp_X]/59 mL; AVENA SATIVA FLOWERING TOP 10 [hp_X]/59 mL; BARIUM CARBONATE 10 [hp_X]/59 mL; TRIBASIC CALCIUM PHOSPHATE 10 [hp_X]/59 mL; CHAMOMILE 10 [hp_X]/59 mL; GELSEMIUM SEMPERVIRENS ROOT 10 [hp_X]/59 mL; NITROGLYCERIN 10 [hp_X]/59 mL; STRYCHNOS IGNATII SEED 10 [hp_X]/59 mL; POTASSIUM ARSENITE ANHYDROUS 10 [hp_X]/59 mL; POTASSIUM PHOSPHATE, DIBASIC 10 [hp_X]/59 mL; HOPS 10 [hp_X]/59 mL; HYDROCHLORIC ACID 10 [hp_X]/59 mL; SODIUM PHOSPHATE, DIBASIC, HEPTAHYDRATE 10 [hp_X]/59 mL; PASSIFLORA INCARNATA FLOWER 10 [hp_X]/59 mL; PHOSPHORUS 10 [hp_X]/59 mL; DELPHINIUM STAPHISAGRIA SEED 10 [hp_X]/59 mL; DATURA STRAMONIUM 10 [hp_X]/59 mL; ARSENIC TRIOXIDE 10 [hp_X]/59 mL
INACTIVE INGREDIENTS: WATER; POTASSIUM SORBATE; CITRIC ACID MONOHYDRATE

Drug Facts

Active Ingredients (per dose)

Aconitum napellus HPUS, Alfalfa HPUS, Argentum nitricum HPUS, Arsenicum Album HPUS, Aurum metallicum HPUS, Avena sativa HPUS, Baryta carbonica HPUS, Calcarea phosphorica HPUS, Chamomilla HPUS, Gelsemium semperivirens HPUS, Glonoinum HPUS, Ignatia amara HPUS, Kali arsenicosum HPUS, Kali phosphoricum HPUS, Lupulus humulus HPUS, Muriaticum acidum HPUS, Natrum phosphoricum HPUS, Passiflora incarnata HPUS, Phosphorus HPUS, Staphysagria HPUS, Stramonium HPUS. Each active ingredient contains equal volumes of 10x, 30x, LM1 potencies. The letters "HPUS" indicate that the components in this product are officially monographed in the Homeopathic Pharmacopoeia of the United States. Product indications are based on Homeopathic Materia Medica.

Purpose

Aconitum napellus HPUS............................Emotional Tension

Alfala HPUS..............................................Gloominess

Argentum nitricum HPUS............................Tremulousness

Arsenicum album HPUS.............................Anguish

Aurum metallicum HPUS............................Hopelessness

Avena Sativa HPUS...................................Nervous Exhaustion

Baryta carbonica HPUS..............................Loss of self-confidence

Calcarea phosphorica HPUS.......................Forgetfullness

Chamomilla HPUS.....................................Impatience

Gelsemium sempervirens HPUS.................Emotional Excitement

Glonoinum HPUS.......................................Extreme irritability

Humulus lupulus HPUS...............................Nervous tremors

Ignatia amara HPUS....................................Hysteria

Kali arsenicosum HPUS..............................Nervousness

Kali phosphoricum HPUS............................Fretfulness

Natrum phosphoricum HPUS.......................Fear

Passiflora incarnata HPUS..........................Abnormal sleep

Phosphorus HPUS.....................................Low spirits

Staphysagria HPUS...................................Emotional sensitivity

Stramonium HPUS....................................Mood Swings

Uses

For the temporary relief of anxiety symptoms including:

- fear
- nervousness
- sensitivity
- minor mood swings
- upset and tightness in stomach and body

Warnings

Ask a doctor before use if

- you are taking any other medications
- you have a medical condition

When using this product, use only as directed.

Stop use and ask a doctor if symptoms persist or worsen.

PREGNANCY OR BREAST FEEDING

If pregnant or breast-feeding, take only on the advice of a physician.

Keep out of the reach of children.

Directions

Dispense Anxietin directly into mouth, or add recommended dosage into 8-12 oz. of purified (non-chlorinated) water and drink. Safe for ages 2 and up.

Dosage By Weight
30-50 lbs 1/2 mL

(13.6-22.6 kg) twice per day

50+ lbs 1 mL

(22.6+ kg) twice per day

Other Information

- do not use if tamper seal is broken
- store in a cool, dry place
- product must not come in contact with metal
- do not store next to electrical devices or appliances

Inactive Ingredients

citric acid, potassium sorbate, purified ionized mineral water

Questions or comments

You can email us at info@hellolife.net or call us toll-free at 1.800.875.0850 Monday through Friday 9am-5pm ET

DESCRIPTION

- 30-day supply
- dropper included
- Anxietin is made without alcohol or sugar. No gluten added.

Mftd for: HelloLife, Inc.
4460 44th St. SE Ste. C-600
Grand Rapids, MI 49512
FDA Pharmaceutical Establishment #1053442, #3009727070
www.anxietin.com

Principal Display Panel

NDC 49726-018-02

ANXIETINTM

Anxiety Symptom Relief

For temporary relief of anxiety symptoms including:

- fear
- nervousness
- sensitivity
- minor mood swings
- upset and tightness in stomach and body

2 FL OZ (59 mL)
Homeopathic (OTC) Medicine